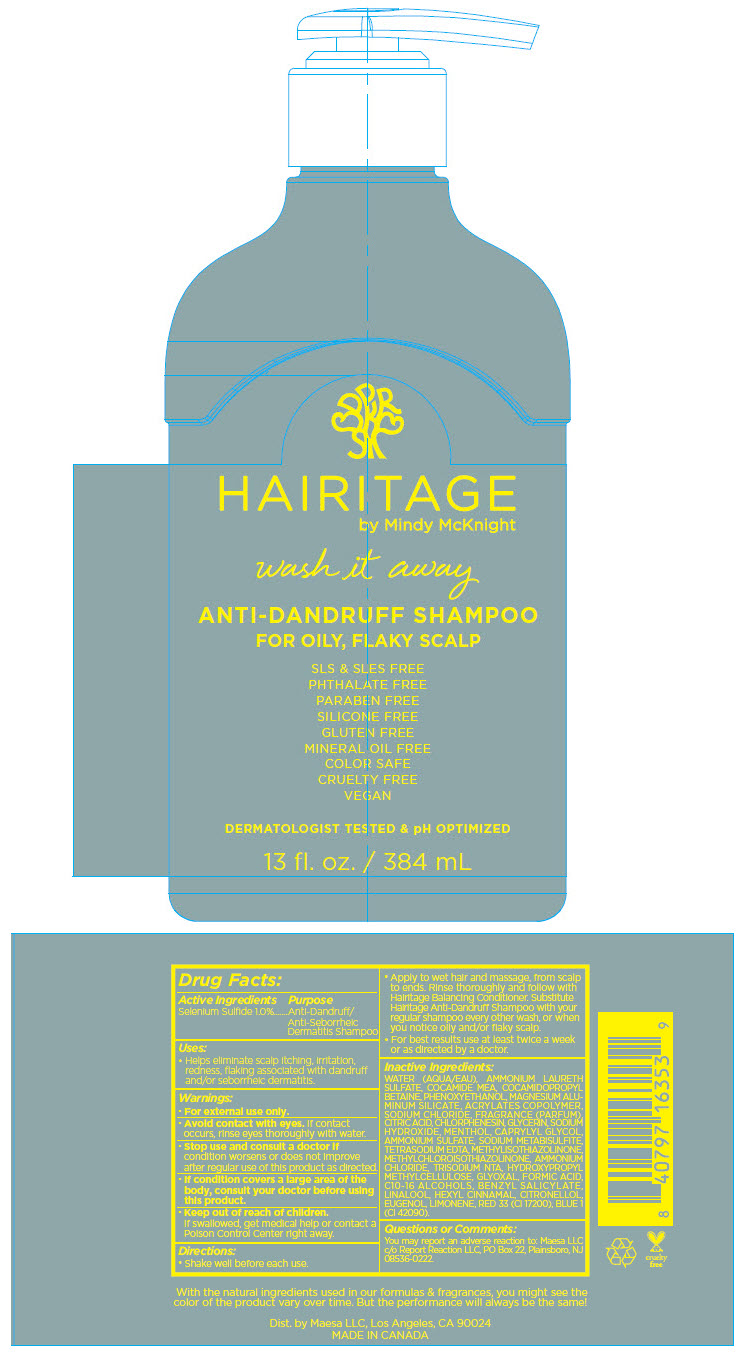 DRUG LABEL: Hairitage Wash It Away Anti-Dandruff for Oily, Flaky Scalp
NDC: 71899-069 | Form: LIQUID
Manufacturer: Maesa, LLC.
Category: otc | Type: HUMAN OTC DRUG LABEL
Date: 20241113

ACTIVE INGREDIENTS: Selenium Sulfide 1 mg/384 mL
INACTIVE INGREDIENTS: Water; MAGNESIUM ALUMINUM SILICATE; AMMONIUM LAURETH-12 SULFATE; Phenoxyethanol; Caprylyl Glycol; Ammonium Lauryl Sulfate; Ammonium Sulfate; Ammonium Chloride; EDETATE SODIUM; Trisodium Nitrilotriacetate; Methylchloroisothiazolinone; Methylisothiazolinone; COCO MONOETHANOLAMIDE; MENTHOL, UNSPECIFIED FORM; Chlorphenesin; Cocamidopropyl Betaine; Sodium Chloride; Glycerin; Sodium Metabisulfite; Sodium Hydroxide; METHACRYLIC ACID - ETHYL ACRYLATE COPOLYMER (4500 MPA.S); CITRIC ACID MONOHYDRATE; HYPROMELLOSE, UNSPECIFIED; Glyoxal; Formic Acid; FD&C BLUE NO. 1; D&C RED NO. 33

Hairitage Wash It Away Anti-Dandruff Shampoo for Oily, Flaky Scalp

Drug Facts:

Active Ingredients

Selenium Sulfide 1.0%

Purpose

Anti-Dandruff/Anti-Seborrheic Dermatitis Shampoo

Uses

- Helps eliminate scalp itching, irritation, redness, flaking associated with dandruff and/or seborrheic dermatitis.

Warnings

- For external use only.
- Avoid contact with eyes. If contact occurs, rinse eyes thoroughly with water.
- Stop use and consult a doctor if condition worsens or does not improve after regular use of this product as directed.
- If condition covers a large area of the body, consult your doctor before using this product.

- Keep out of reach of children.
  If swallowed, get medical help or contact a Poison Control Center right away.

Directions

- Shake well before each use.
- Apply to wet hair and massage, from scalp to ends. Rinse thoroughly and follow with Hairitage Balancing Conditioner. Substitute Hairitage Anti-Dandruff Shampoo with your regular shampoo every other wash, or when you notice oily and/or flaky scalp.
- For best results use at least twice a week or as directed by a doctor.

Inactive Ingredients

WATER (AQUA/EAU), AMMONIUM LAURETH SULFATE, COCAMIDE MEA, COCAMIDOPROPYL BETAINE, PHENOXYETHANOL, MAGNESIUM ALUMINUM SILICATE, ACRYLATES COPOLYMER, SODIUM CHLORIDE, FRAGRANCE (PARFUM), CITRIC ACID, CHLORPHENESIN, GLYCERIN, SODIUM HYDROXIDE, MENTHOL, CAPRYLYL GLYCOL, AMMONIUM SULFATE, SODIUM METABISULFITE, TETRASODIUM EDTA, METHYLISOTHIAZOLINONE, METHYLCHLOROISOTHIAZOLINONE, AMMONIUM CHLORIDE, TRISODIUM NTA, HYDROXYPROPYL METHYLCELLULOSE, GLYOXAL, FORMIC ACID, C10-16 ALCOHOLS, BENZYL SALICYLATE, LINALOOL, HEXYL CINNAMAL, CITRONELLOL, EUGENOL, LIMONENE, RED 33 (CI 17200), BLUE 1 (CI 42090).

Questions or Comments

You may report an adverse reaction to: Maesa LLC c/o Report Reaction LLC, PO Box 22, Plainsboro, NJ 08536-0222.

Dist. by Maesa LLC, Los Angeles, CA 90024

PRINCIPAL DISPLAY PANEL - 384 mL Bottle Label

HAIRITAGE
by Mindy McKnight

wash it away

ANTI-DANDRUFF SHAMPOO
FOR OILY, FLAKY SCALP

SLS & SLES FREE
PHTHALATE FREE
PARABEN FREE
SILICONE FREE
GLUTEN FREE
MINERAL OIL FREE
COLOR SAFE
CRUELTY FREE
VEGAN

DERMATOLOGIST TESTED & pH OPTIMIZED

13 fl. oz. / 384 mL